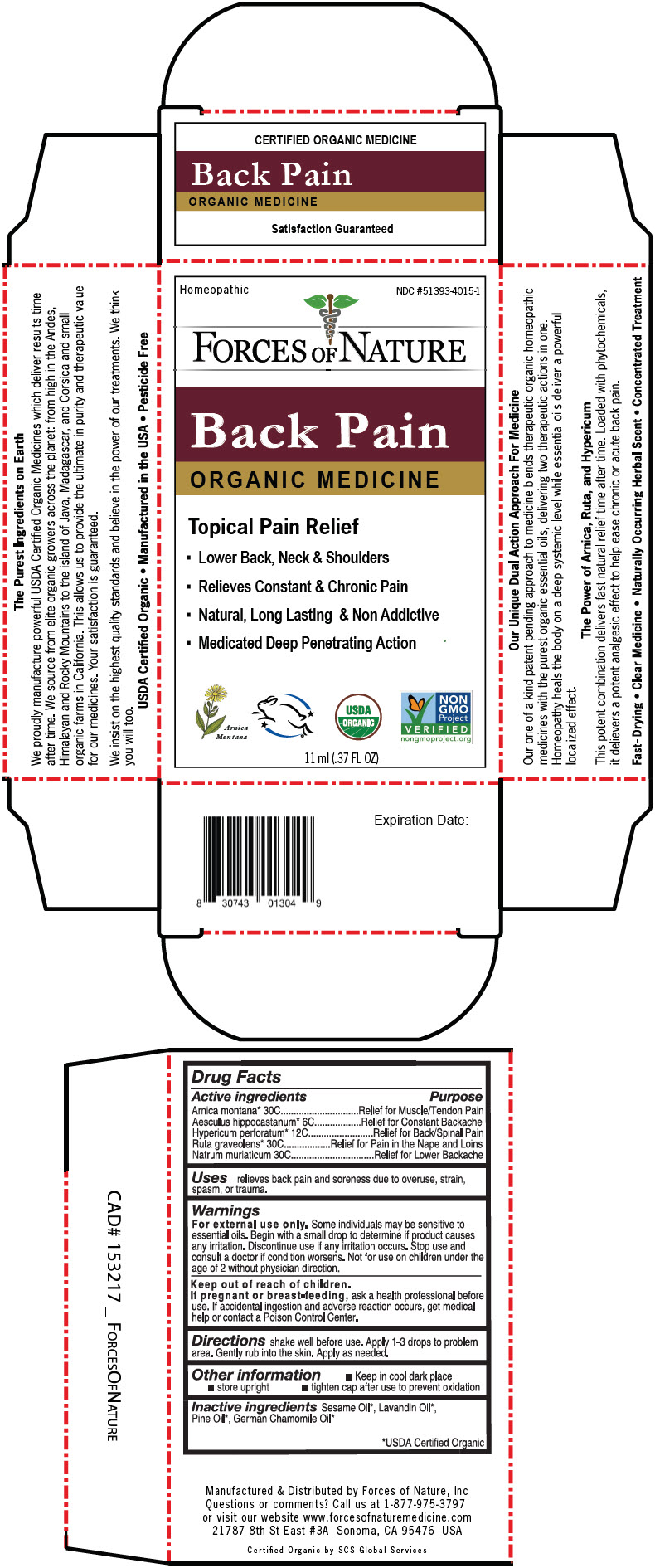 DRUG LABEL: Back Pain
NDC: 51393-4015 | Form: SOLUTION/ DROPS
Manufacturer: Forces of Nature
Category: homeopathic | Type: HUMAN OTC DRUG LABEL
Date: 20260220

ACTIVE INGREDIENTS: ARNICA MONTANA WHOLE 30 [hp_C]/100 mL; HORSE CHESTNUT 6 [hp_C]/100 mL; HYPERICUM PERFORATUM WHOLE 12 [hp_C]/100 mL; RUTA GRAVEOLENS WHOLE 30 [hp_C]/100 mL; SODIUM CHLORIDE 30 [hp_C]/100 mL
INACTIVE INGREDIENTS: SESAME OIL; LAVANDIN OIL; PINE NEEDLE OIL (PINUS SYLVESTRIS); CHAMOMILE FLOWER OIL

Back Pain
Pain Management

Drug Facts

ACTIVE INGREDIENT

Active ingredients | Purpose
Arnica montana [USDA Certified Organic] 30C | Relief for Muscle/Tendon Pain
Aesculus hippocastanum 6C | Relief for Constant Backache
Hypericum perforatum 12C | Relief for Back/Spinal Pain
Ruta graveolens 30C | Relief for Pain in the Nape and Loins
Natrum muriaticum 30C | Relief for Lower Backache

Uses

relieves back pain and soreness due to overuse, strain, spasm, or trauma.

Warnings

For external use only.Some individuals may be sensitive to essential oils. Begin with a small drop to determine if product causes any irritation. Discontinue use if any irritation occurs. Stop use and consult a doctor if condition worsens. Not for use on children under the age of 2 without physician direction.

Keep out of reach of children.

PREGNANCY OR BREAST FEEDING

If pregnant or breast-feeding,ask a health professional before use. If accidental ingestion and adverse reaction occurs, get medical help or contact a Poison Control Center.

Directions

shake well before use. Simply roll on the problem area. Gently rub into the skin. Apply as needed.

Other information

- Keep in cool dark place
- store upright
- tighten cap after use to prevent oxidation

Inactive ingredients

Sesame Oil , Lavandin Oil , Pine Oil , German Chamomile Oil

Questions or comments?

Call us at 1-877-975-3797 or visit our website www.forcesofnaturemedicine.com

Manufactured & Distributed by Forces of Nature, Inc

PRINCIPAL DISPLAY PANEL - 11 ml Bottle Carton

Homeopathic
NDC #51393-4015-1

FORCES OF NATURE

Back Pain

ORGANIC MEDICINE

Topical Pain Relief

- Lower Back, Neck & Shoulders
- Relieves Constant & Chronic Pain
- Natural, Long Lasting & Non Addictive
- Medicated Deep Penetrating Action

Arnica
Montana

USDA
ORGANIC

NON
GMO
Project
VERIFIED
nongmoproject.org

11 ml (.37 FL OZ)